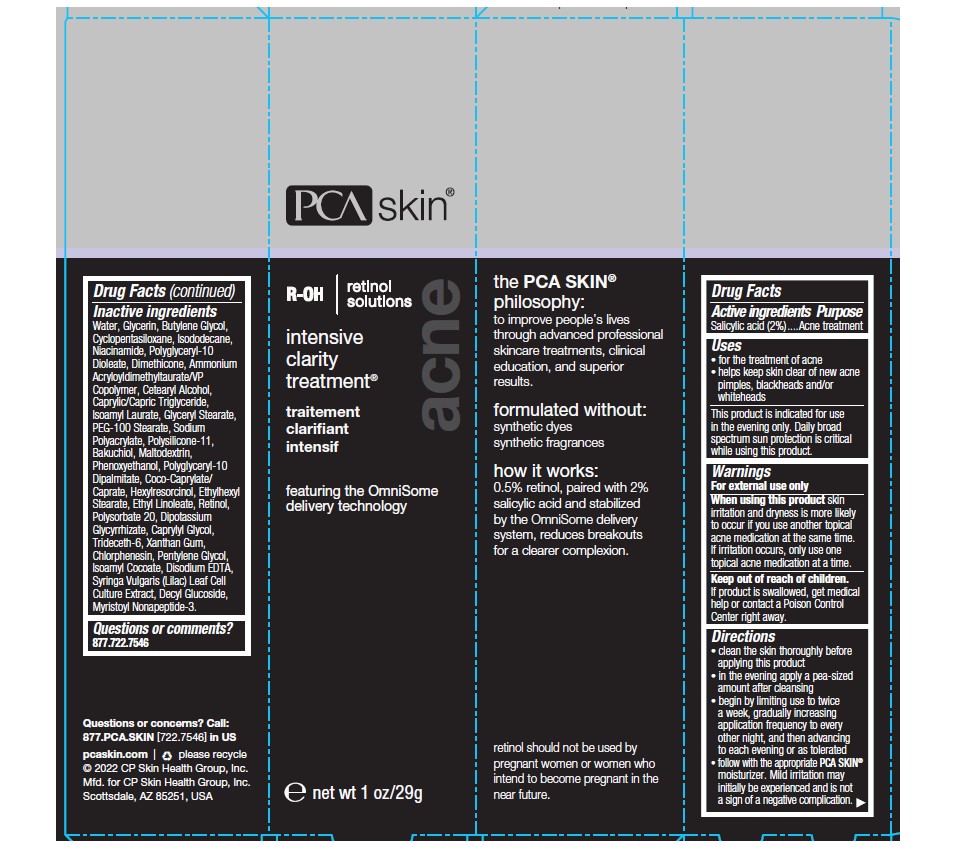 DRUG LABEL: PCA SKIN Intensive Clarity Treatment
NDC: 68726-359 | Form: GEL
Manufacturer: CP Skin Health Group, Inc.
Category: otc | Type: HUMAN OTC DRUG LABEL
Date: 20241203

ACTIVE INGREDIENTS: SALICYLIC ACID 2 g/100 g
INACTIVE INGREDIENTS: GLYCERIN; PEG-12 GLYCERYL DIMYRISTATE; CYCLOMETHICONE 5; ISODODECANE; NIACINAMIDE; BUTYLENE GLYCOL; DIMETHICONE; AMMONIUM ACRYLOYLDIMETHYLTAURATE/VP COPOLYMER; CETOSTEARYL ALCOHOL; ISOAMYL LAURATE; GLYCERYL MONOSTEARATE; PEG-100 STEARATE; DIMETHICONE/VINYL DIMETHICONE CROSSPOLYMER (SOFT PARTICLE); SODIUM POLYACRYLATE (8000 MW); WATER; BAKUCHIOL; MEDIUM-CHAIN TRIGLYCERIDES; MALTODEXTRIN; PHENOXYETHANOL; COCO-CAPRYLATE; RETINOL; ETHYLHEXYL STEARATE; ETHYL LINOLEATE; HEXYLRESORCINOL; POLYSORBATE 20; GLYCYRRHIZINATE DIPOTASSIUM; CAPRYLYL GLYCOL; XANTHAN GUM; CHLORPHENESIN; TRIDECETH-6; PENTYLENE GLYCOL; ISOAMYL COCOATE; SYRINGA VULGARIS FLOWER; SODIUM CITRATE; EDETATE DISODIUM; DECYL GLUCOSIDE; CITRIC ACID MONOHYDRATE; MYRISTOYL PENTAPEPTIDE-4

PCA SKIN Intensive Clarity Treatment

Active Ingredient

Salicylic Acid (2.0%)

Purpose

Acne Treatment

Uses

For the treatment of acne. Helps keep skin clear of new acne pimples, blackheads and/or whiteheads.

Warnings

For external use only

When using this product

Skin irritation and dryness is more likely to occur if you use another topical acne medication at the same time. If irritation occurs, only use one topical acne medication at a time.

Keep out of reach of children.

If swallowed, get medical help or contact a Poison Control Center right away.

Directions

- Cleanse the skin thoroughly before applying this product.
- Cover the entire affected area with a thin layer one to three times daily.
- Because excessive drying of the skin may occur, start with one application daily, then gradually increase to two or three times daily if needed or as directed by a doctor.
- If bothersome dryness or peeling occurs, reduce application to once daily or every other day.

Inactive Ingredients

Water, Glycerin, PEG-12 Glyceryl Dimyristate, Cyclopentasiloxane, Isododecane, Niacinamide, Butylene Glycol, Dimethicone, Ammonium Acryloyldimethyltaurate/VP Copolymer, Cetearyl Alcohol, Isoamyl Laurate, Glyceryl Stearate, PEG-100 Stearate, Sodium Polyacrylate,
Polysilicone-11, Bakuchiol, Caprylic/Capric Triglyceride, Maltodextrin, Phenoxyethanol, Coco-Caprylate/Caprate, Hexyl Resorcinol, Ethylhexyl Stearate, Retinol, Ethyl Linoleate, Polysorbate 20, Hexylresorcinol, Dipotassium Glycrrhizinate, Caprylyl Glycol, Trideceth-6, Xanthan Gum, Chlorphenesin, Pentylene Glycol, Isoamyl Cocoate, Syringa Vulgaris (Lilac) Leaf Cell Culture Extract, Sodium Citrate, Disodium EDTA, Decyl Glucoside, Myristoyl Nonapeptide-3, Citric Acid